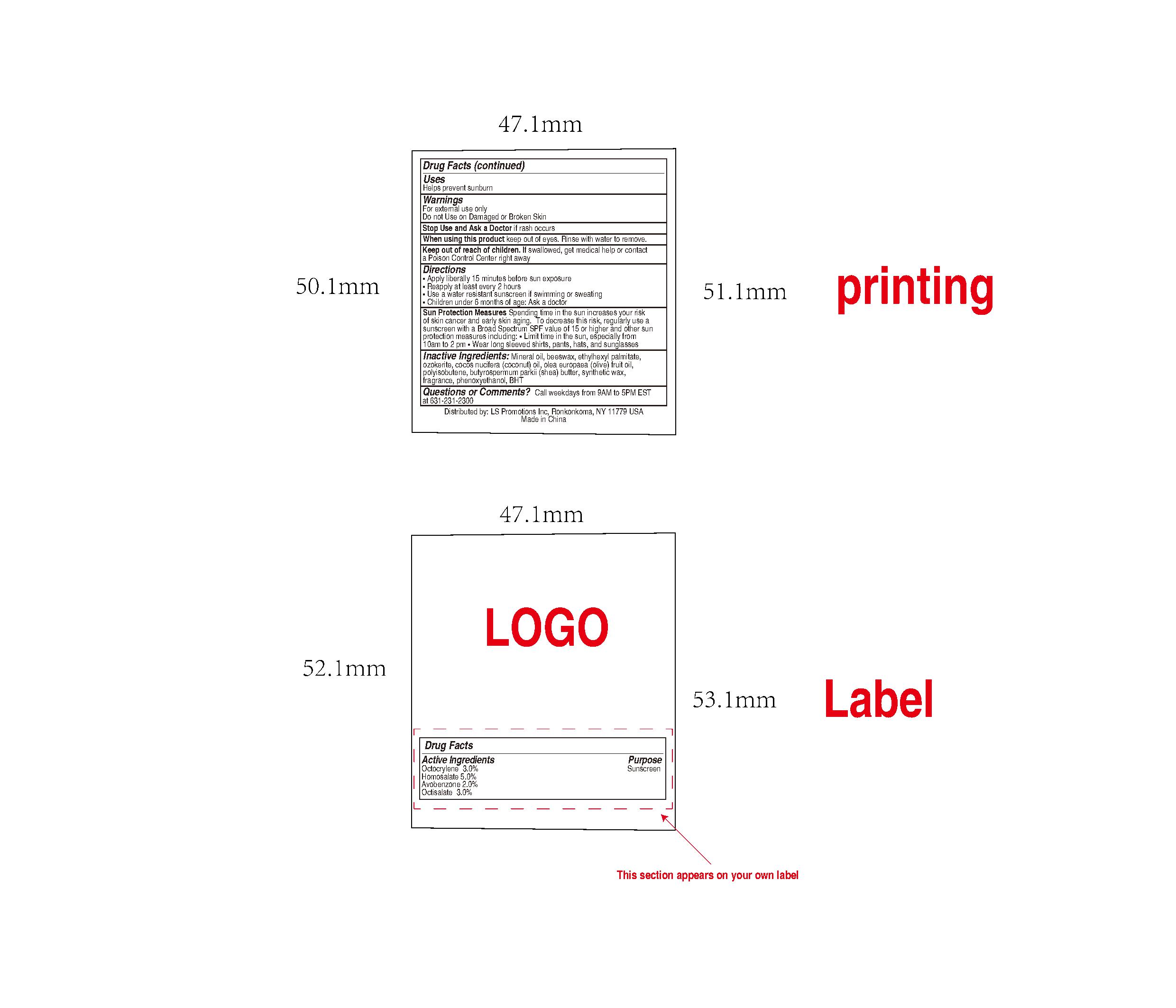 DRUG LABEL: natural lip balm SPF15( chocolate sundae)
NDC: 82953-044 | Form: LIPSTICK
Manufacturer: Cosmuses Cosmetics (Ningbo) Co., Ltd.
Category: otc | Type: HUMAN OTC DRUG LABEL
Date: 20250331

ACTIVE INGREDIENTS: OCTOCRYLENE 3 g/100 g; HOMOSALATE 5 g/100 g; AVOBENZONE 2 g/100 g; OCTISALATE 3 g/100 g
INACTIVE INGREDIENTS: BHT; MINERAL OIL; BEESWAX; ETHYLHEXYL PALMITATE; CERESIN; PHENOXYETHANOL; FRAGRANCE CHOCOLATE ORC1600599; SYNTHETIC WAX (1800 MW); POLYISOBUTYLENE (1000 MW); COCOS NUCIFERA (COCONUT) OIL; OLEA EUROPAEA FRUIT VOLATILE OIL; BUTYROSPERMUM PARKII (SHEA) BUTTER

natural lip balm SPF15 (chocolate sundae LB100FCH)

Drug Facts

Active ingredients

Octocrylene 3%

Homosalate 5%

Avobenzone 2%

Octisalate 3%

Purpose

Sunscreen

Uses

- Helps prevent sunburn

Warnings

For external use only

WARNINGS

For external use only

Do not use on damaged or broken skin.

Stop use and ask a doctor if rash occurs.

When using this product keep out of eyes. Rinse with water to remove.

Keep out of reach of children. If swallowed, get medical help or contact a Poison Control Center right away.

Directions

- Apply liberally 15minutes before sun exposure
- Reapply at least every 2 hours.
- Use a water resistant sunscreen if swimming or sweating.
- Children under 6 months of age: Ask a doctor.

OTHER SAFETY INFORMATION

Sun Protection Measures

Spending time in the sun increases your risk of skin cancer and early skin aging.

To decreases this risk, regularly use a sunscreen with a Broad Spectrum SPF value of 15 or higher and other sun protection measures including:

limit time in the sun, especially from 10a.m.- 2p.m.
wear long-sleeve shirts, pants, hats and sunglasses

Inactive ingredients

Mineral Oil, Beeswax, Ethylhexyl Palmitate, Ozokerite, Cocos Nucifera (Coconut) Oil,Olea Europaea (Olive) Fruit Oil,Polyisobutene, Butyrospermum Parkii (Shea) Butter, Synthetic Wax, Phenoxyethanol,Fragrance, BHT

Questions or Comments?

Call weekdays from 9AM to 5PM EST at 631-231-2300